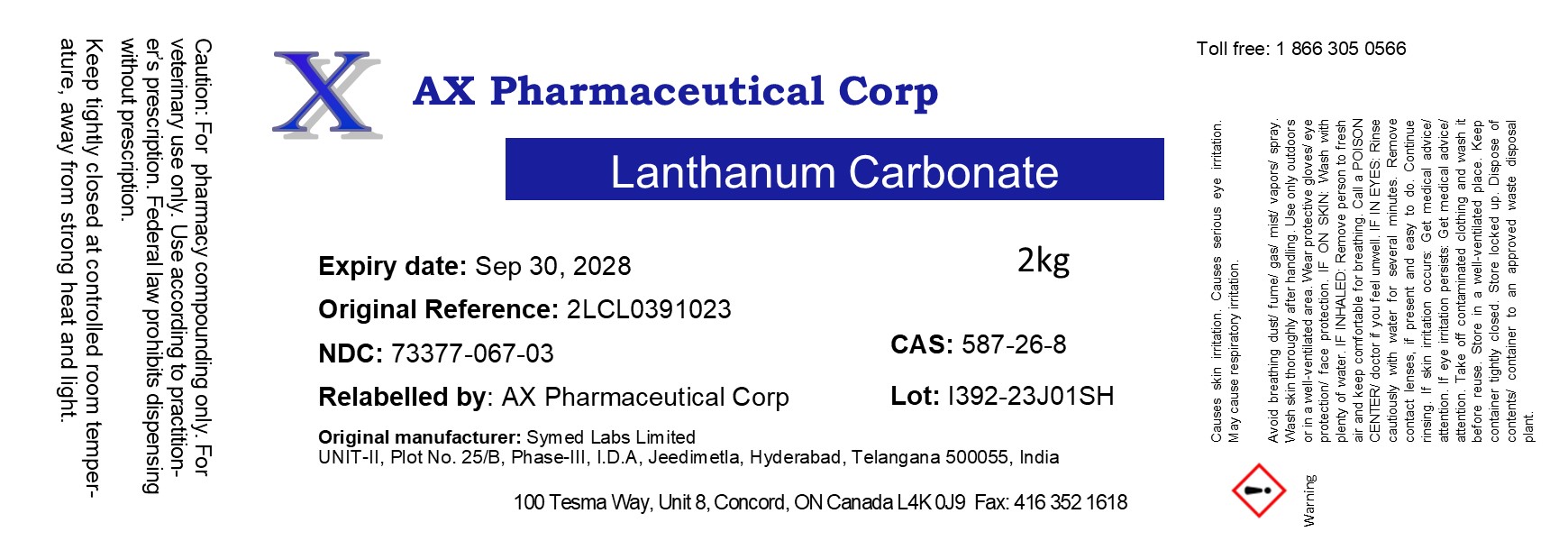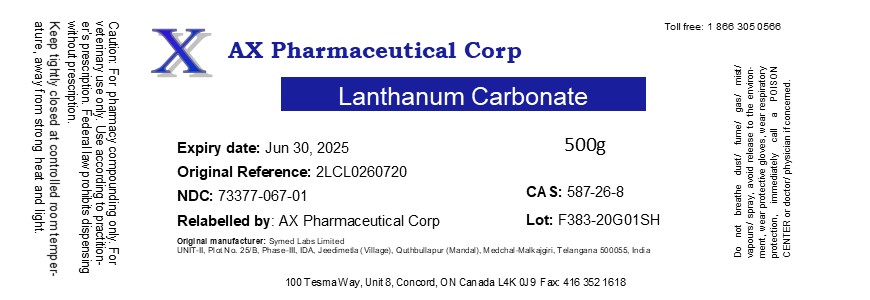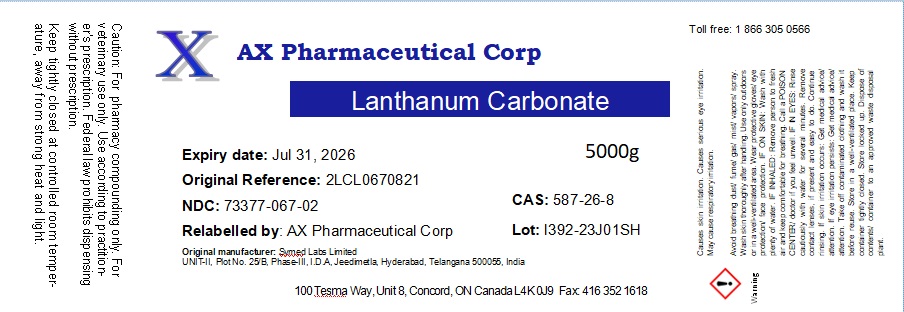 DRUG LABEL: Lanthanum Carbonate
NDC: 73377-067 | Form: POWDER
Manufacturer: AX Pharmaceutical Corp
Category: other | Type: BULK INGREDIENT - ANIMAL DRUG
Date: 20241101

ACTIVE INGREDIENTS: LANTHANUM CARBONATE 1 g/1 g

Lanthanum Carbonate